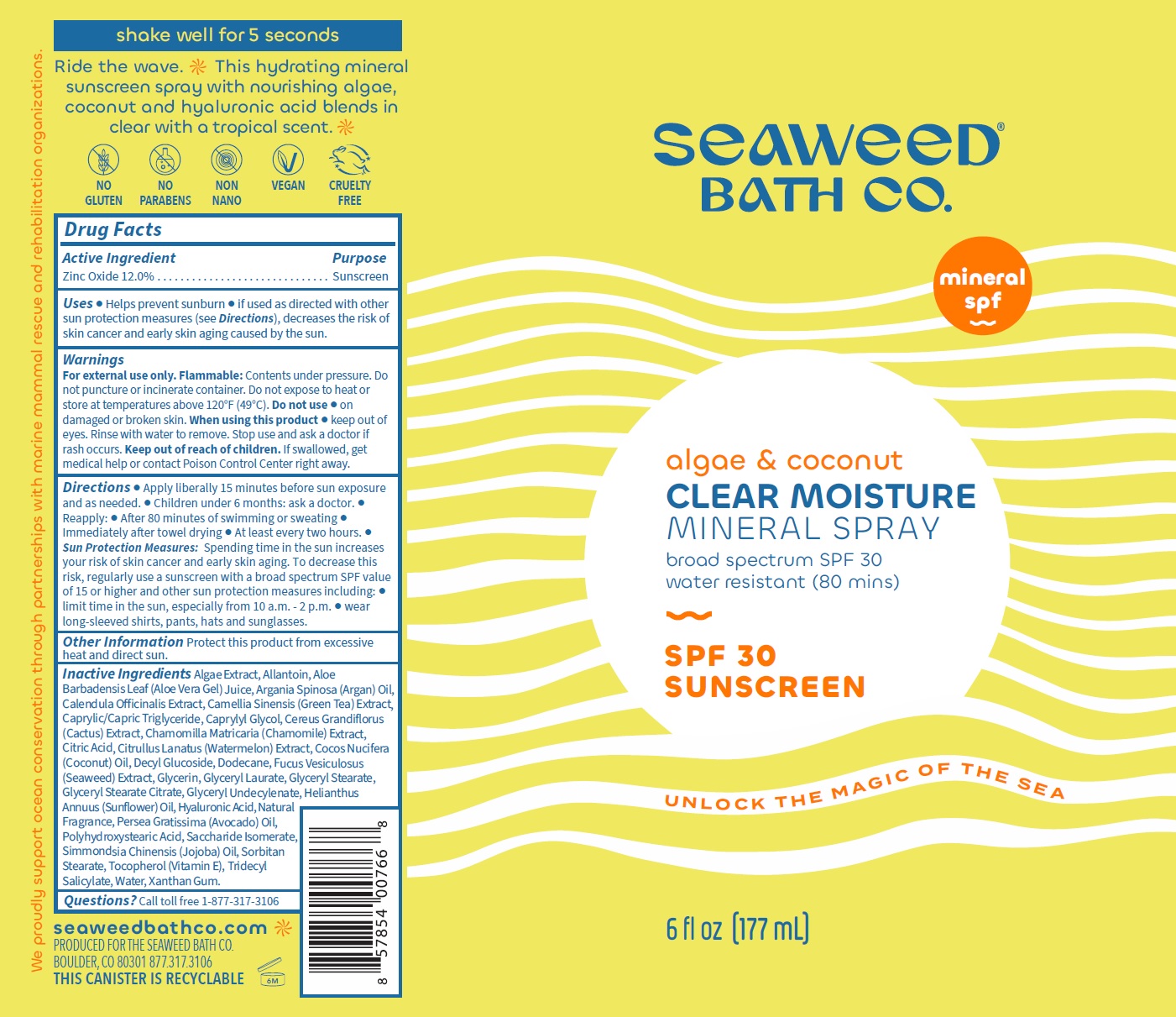 DRUG LABEL: SEAWEED BATH CO. Clear Moisture Mineral SPF-30
NDC: 81159-393 | Form: SOLUTION
Manufacturer: The Seaweed Bath Co.
Category: otc | Type: HUMAN OTC DRUG LABEL
Date: 20231106

ACTIVE INGREDIENTS: ZINC OXIDE 120 mg/1 mL
INACTIVE INGREDIENTS: ALLANTOIN; ALOE VERA LEAF; ARGAN OIL; CALENDULA OFFICINALIS FLOWER; GREEN TEA LEAF; MEDIUM-CHAIN TRIGLYCERIDES; CAPRYLYL GLYCOL; CHAMOMILE; CITRIC ACID MONOHYDRATE; WATERMELON; COCONUT OIL; DECYL GLUCOSIDE; DODECANE; FUCUS VESICULOSUS; GLYCERIN; GLYCERYL LAURATE; GLYCERYL MONOSTEARATE; GLYCERYL STEARATE CITRATE; HELIANTHUS ANNUUS FLOWERING TOP; HYALURONIC ACID; AVOCADO OIL; SACCHARIDE ISOMERATE; JOJOBA OIL; SORBITAN MONOSTEARATE; TOCOPHEROL; TRIDECYL SALICYLATE; WATER; XANTHAN GUM

SEAWEED BATH CO. Clear Moisture Mineral Spray SPF-30

Active Ingredient

Zinc Oxide 12.0%

Purpose

Sunscreen

Uses

• Helps prevent sunburn • If used as directed with other sun protection measures (see), decreases the risk of skin cancer and early skin aging caused by the sun. Directions

Warnings

Contents under pressure. Do not puncture or incinerate container. Do not expose to heat or store at temperatures above 120°F (49°C). For external use only. Flammable:

Do not use

• on damaged or broken skin.

When using this product

• keep out of eyes. Rinse with water to remove. Stop use and ask a doctor if rash occurs.

Keep out of reach of children.

If swallowed, get medical help or contact Poison Control Center right away.

Directions

• Apply liberally 15 minutes before sun exposure and as needed. • Children under 6 months: ask a doctor. • Reapply: • After 80 minutes of swimming or sweating • Immediately after towel drying • At least every two hours.

• Spending time in the sun increases your risk of skin cancer and early skin aging. To decrease this risk, regularly use a sunscreen with a broad spectrum SPF value of 15 or higher and other sun protection measures including: • limit time in the sun, especially from 10 a.m. - 2 p.m. • wear long-sleeved shirts, pants, hats and sunglasses. Sun Protection Measures:

Other Information

Protect this product from excessive heat and direct sun.

Inactive Ingredients

Algae Extract, Allantoin, Aloe Barbadensis Leaf (Aloe Vera Gel) Juice, Argania Spinosa (Argan) Oil, Calendula Officinalis Extract, Camellia Sinensis (Green Tea) Extract, Caprylic/Capric Triglyceride, Caprylyl Glycol, Cereus Grandiflorus (Cactus) Extract, Chamomilla Matricaria (Chamomile) Extract, Citric Acid, Citrullus Lanatus (Watermelon) Extract, Cocos Nucifera (Coconut) Oil, Decyl Glucoside, Dodecane, Fucus Vesiculosus (Seaweed) Extract, Glycerin, Glyceryl Laurate, Glyceryl Stearate, Glyceryl Stearate Citrate, Glyceryl Undecylenate, Helianthus Annuus (Sunflower) Oil, Hyaluronic Acid, Natural Fragrance, Persea Gratissima (Avocado) Oil, Polyhydroxystearic Acid, Saccharide Isomerate, Simmondsia Chinensis (Jojoba) Oil, Sorbitan Stearate, Tocopherol (Vitamin E), Tridecyl Salicylate, Water, Xanthan Gum.

Questions?

Call toll free 1-877-317-3106